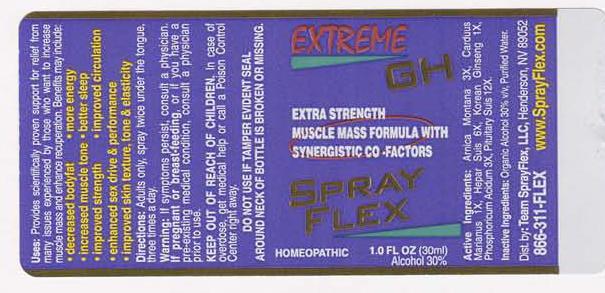 DRUG LABEL: Extreme GH
NDC: 50845-0036 | Form: SPRAY
Manufacturer: Liddell Laboratories
Category: homeopathic | Type: HUMAN OTC DRUG LABEL
Date: 20100826

ACTIVE INGREDIENTS: ARNICA MONTANA 1 [hp_X]/1 mL; SILYBUM MARIANUM SEED 1 [hp_X]/1 mL; PORK LIVER 4 [hp_X]/1 mL; ASIAN GINSENG 1 [hp_X]/1 mL; PHOSPHORIC ACID 1 [hp_X]/1 mL; SUS SCROFA PITUITARY GLAND 10 [hp_X]/1 mL
INACTIVE INGREDIENTS: WATER; ALCOHOL

Extreme GH

ACTIVE INGREDIENT

ACTIVE INGREDIENTS: Arnica montana 3X, Carduus marianus 1X, Hepar suis 6X, Korean ginseng 1X, Phosphoricum acidum 3X, Pituitary suis 12X.

PURPOSE

USES: Provides scientifically proven support for relief from many issues experienced by those who want to increase muscle mass and enhance recuperation. Benefits may include: *decreased bodyfat *more energy *increased muscle tone *better sleep *improved strength *improved circulation *enhanced sex drive and performance *improved skin texture, tone and elasticity

WARNINGS

WARNINGS: If symptoms persist, consult a physician. If pregnant or breast-feeding, or if you have a pre-existing medical condition, consult a physician prior to use.

DO NOT USE IF TAMPER EVIDENT SEAL AROUND NECK OF BOTTLE IS BROKEN OR MISSING.

DOSAGE AND ADMINISTRATION

DIRECTIONS: Adults only, spray twice under the tongue, three times a day.

INACTIVE INGREDIENT

INACTIVE INGREDIENTS: Organic alcohol 30% v/v, Purified water.

KEEP OUT OF REACH OF CHILDREN: In case of overdose, get medical help or call a Poison Control Center right away.

INDICATIONS AND USAGE

USES: Provides scientifically proven support for relief from many issues experienced by those who want to increase muscle mass and enhance recuperation. Benefits may include: *decreased bodyfat *more energy *increased muscle tone *better sleep *improved strength *improved circulation *enhanced sex drive and performance *improves skin texture, tone and elasticity

QUESTIONS

Dist. by:

Team SprayFlex, LLC

Henderson, NV 89052

866-311-FLEX

www.SprayFlex.com

PACKAGE LABEL

EXTREME GH

EXTRA STRENGTH

MUSCLE MASS FORMULA WITH SYNERGISTIC CO-FACTORS

SPRAYFLEX

HOMEOPATHIC

1.0 FL OZ (30 ml)